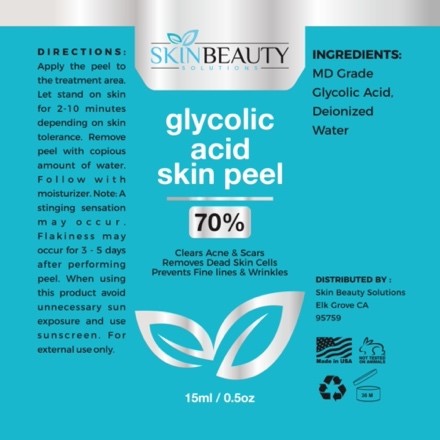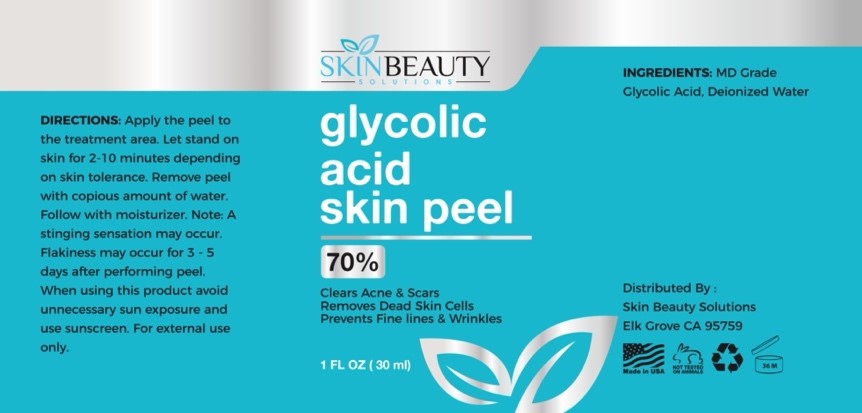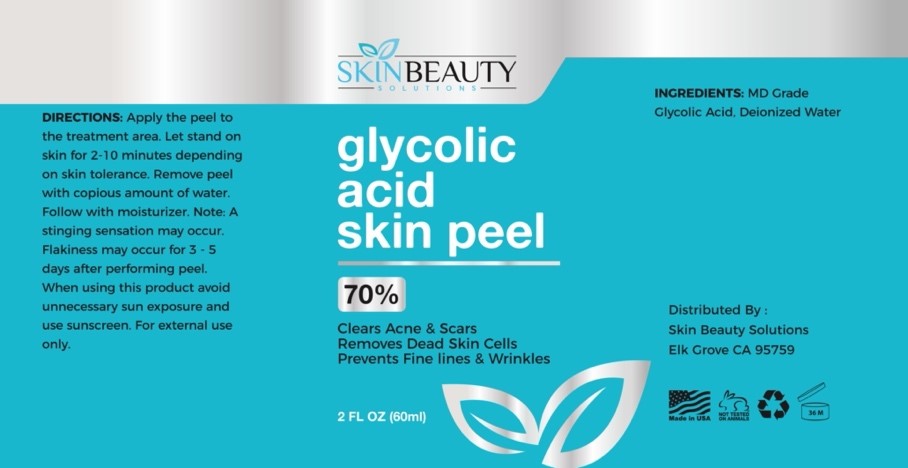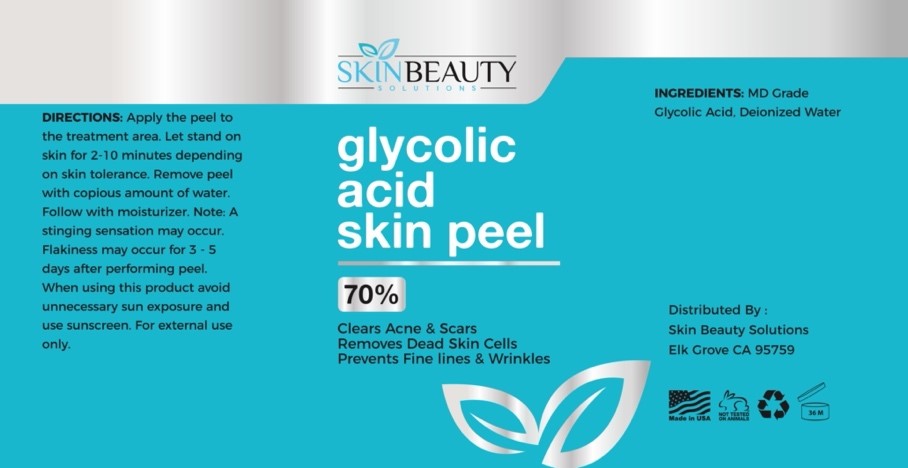 DRUG LABEL: GLYCOLIC Acid 70 Skin Chemical Peel
NDC: 84785-0026 | Form: SOLUTION
Manufacturer: Gazebo Wellness SKIN LLC
Category: otc | Type: HUMAN OTC DRUG LABEL
Date: 20241216

ACTIVE INGREDIENTS: GLYCOLIC ACID 0.3 mg/30 mL
INACTIVE INGREDIENTS: WATER

DOSAGE AND ADMINISTRATION

DIRECTIONS: Apply the peel to the treatment area. Let stand on skin for 2-10 minutes depending on skin tolerance. Remove peel with copious amount of water. Follow with moisturizer. Note: A stinging sensation may occur. Flakiness may occur for 3-5 days after performing peel. When using this product avoid unnecessary sun exposure and

WARNINGS

DIRECTIONS: Apply the peel to the treatment area. Let stand on skin for 2-10 minutes depending on skin tolerance. Remove peel with copious amount of water. Follow with moisturizer. Note: A stinging sensation may occur. Flakiness may occur for 3-5 days after performing peel. When using this product avoid unnecessary sun exposure and

Inactive ingredient: Deionized Water.

INDICATIONS AND USAGE

Apply the peel to the treatment area. Let stand on skin for 2-10 minutes depending on skin tolerance. Remove peel with copious amount of water. Follow with moisturizer. Note: A stinging sensation may occur. Flakiness may occur for 3-5 days after performing peel. When using this product avoid unnecessary sun exposure and
use sunscreen. For external use only.

keep out of reach of children

PURPOSE

glycolic acid skin peel
35%
Clears Acne & Scars Removes Dead Skin Cells Prevents Fine lines & Wrinkles

Distributed By:
Skin Beauty Solutions Elk Grove CA 95759

Active ingredient: MD Grade Glycolic Acid.

PACKAGE LABEL

Content of labeling